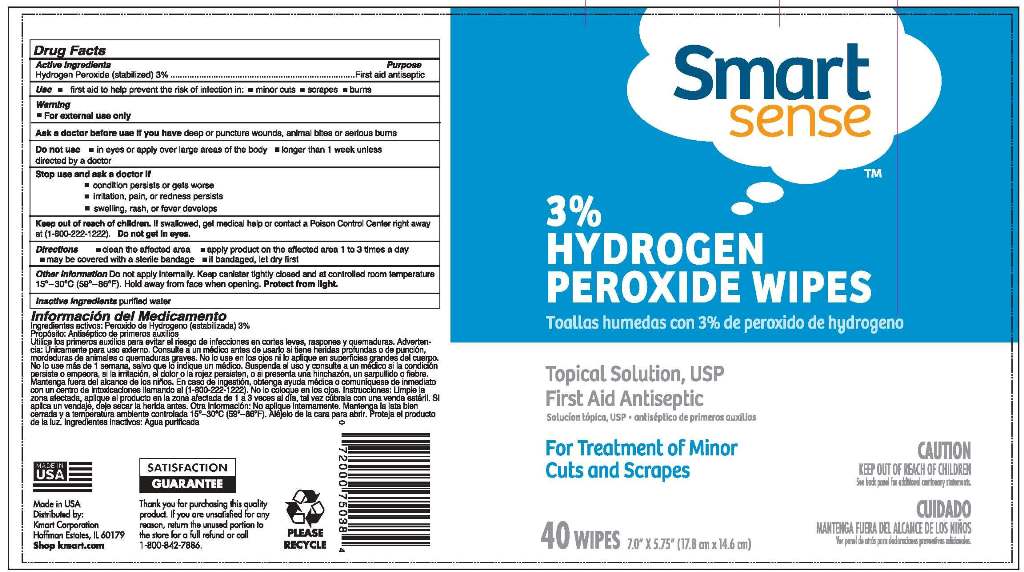 DRUG LABEL: SMART SENSE Hydrogen Peroxide
NDC: 52553-002 | Form: CLOTH
Manufacturer: US Nonwovens
Category: otc | Type: HUMAN OTC DRUG LABEL
Date: 20111003

ACTIVE INGREDIENTS: HYDROGEN PEROXIDE 0.03 mL/1 mL
INACTIVE INGREDIENTS: WATER

SMART SENSE Hydrogen Peroxide Wipes

PACKAGE LABEL

Smart Sense

3% Hydrogen Peroxide Wipes

Topical Solution, USP

First Aid Antiseptic

For Treatment of Minor Cuts and Scrapes

CAUTION
KEEP OUT OF REACH OF CHILDREN

40 Wipes

7.0" X 5.75"

DRUG FACTS

Active Ingredients

Hydrogen Peroxide (stabilized) 3%

Purpose

First aid antiseptic

INDICATIONS AND USAGE

Use - first aid to help prevent the risk of infection in; - minor cuts - scrapes - burns

WARNINGS

For external use only

Ask a doctor before use if you have deep or puncture wounds, animal bites or serious burns

Do not use - in eyes or over large areas of the body - longer than 1 week unless directed by a doctor

Stop use and ask a doctor if

- condition persists or gets worse

- irritation, pain, or redness persists

- swelling, rash, or fever develops

Keep out of reach of children. If swallowed, get medical help or contact a Poison Control Center right away

at (1-800-222-1222). Do not get in eyes.

DOSAGE AND ADMINISTRATION

Directions - clean the affected area - apply product on the affected area 1 to 3 times a day

- may be covered with a sterile bandage - if bandaged, let dry first

Other information. Do not apply internally. Keep canister tightly closed and at a controlled room temperature

15^0 - 30^0C (58^0 - 86^0F). Hold away from face when opening. Protect from light.

Inactive ingredients purified water

PACKAGE LABEL

Made in USA

Distributed by:

Kmart Corporation

Hoffman Estates. IL 60170

Shop kmart.com